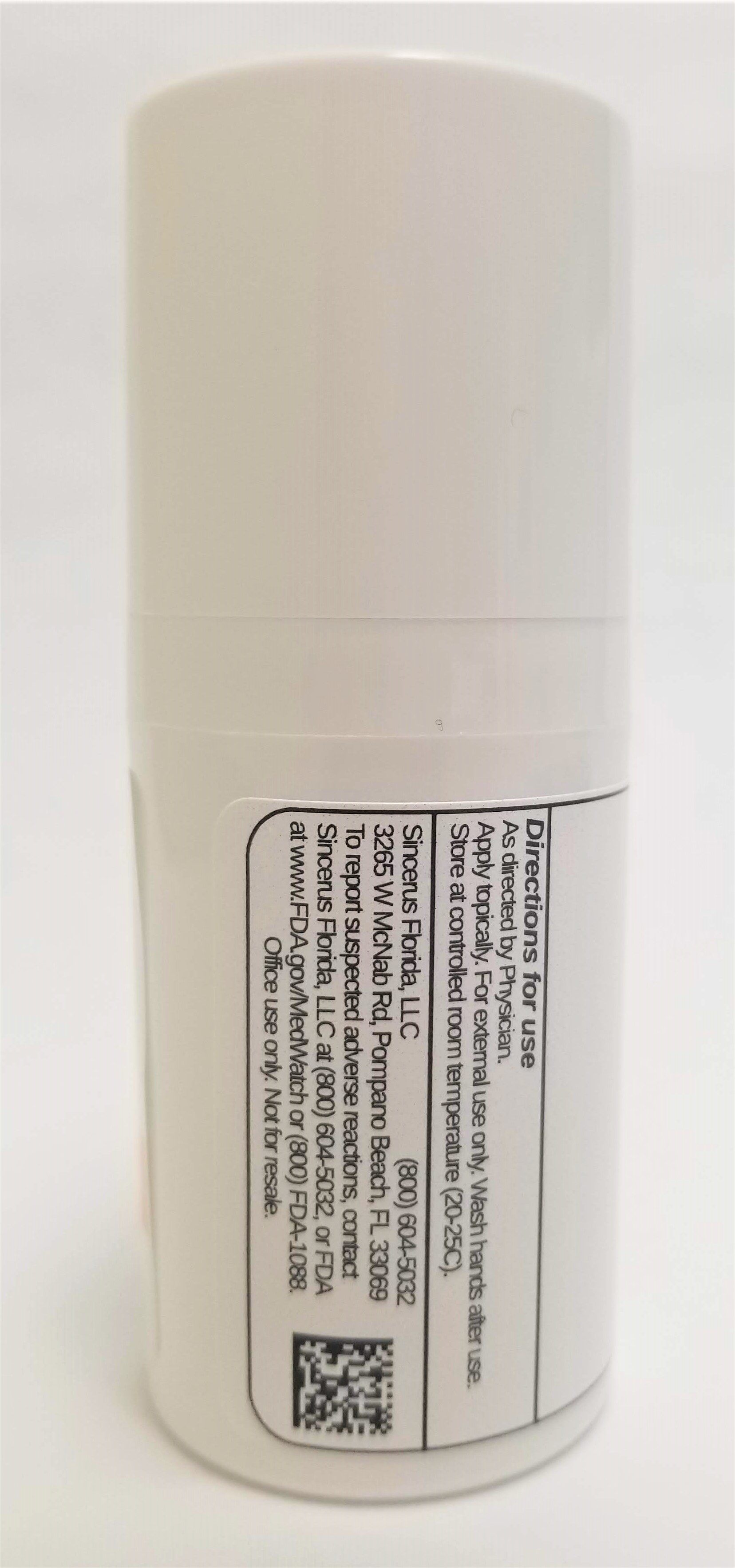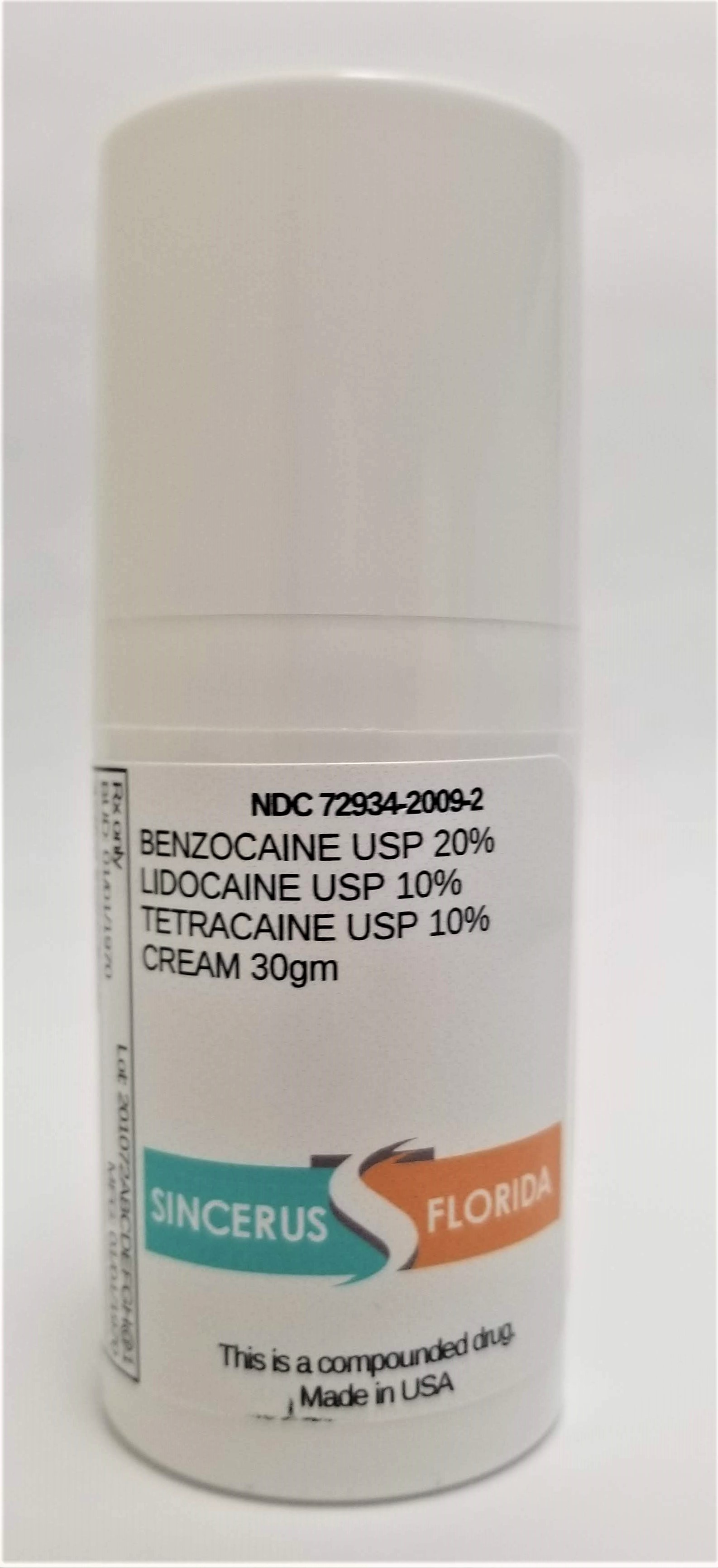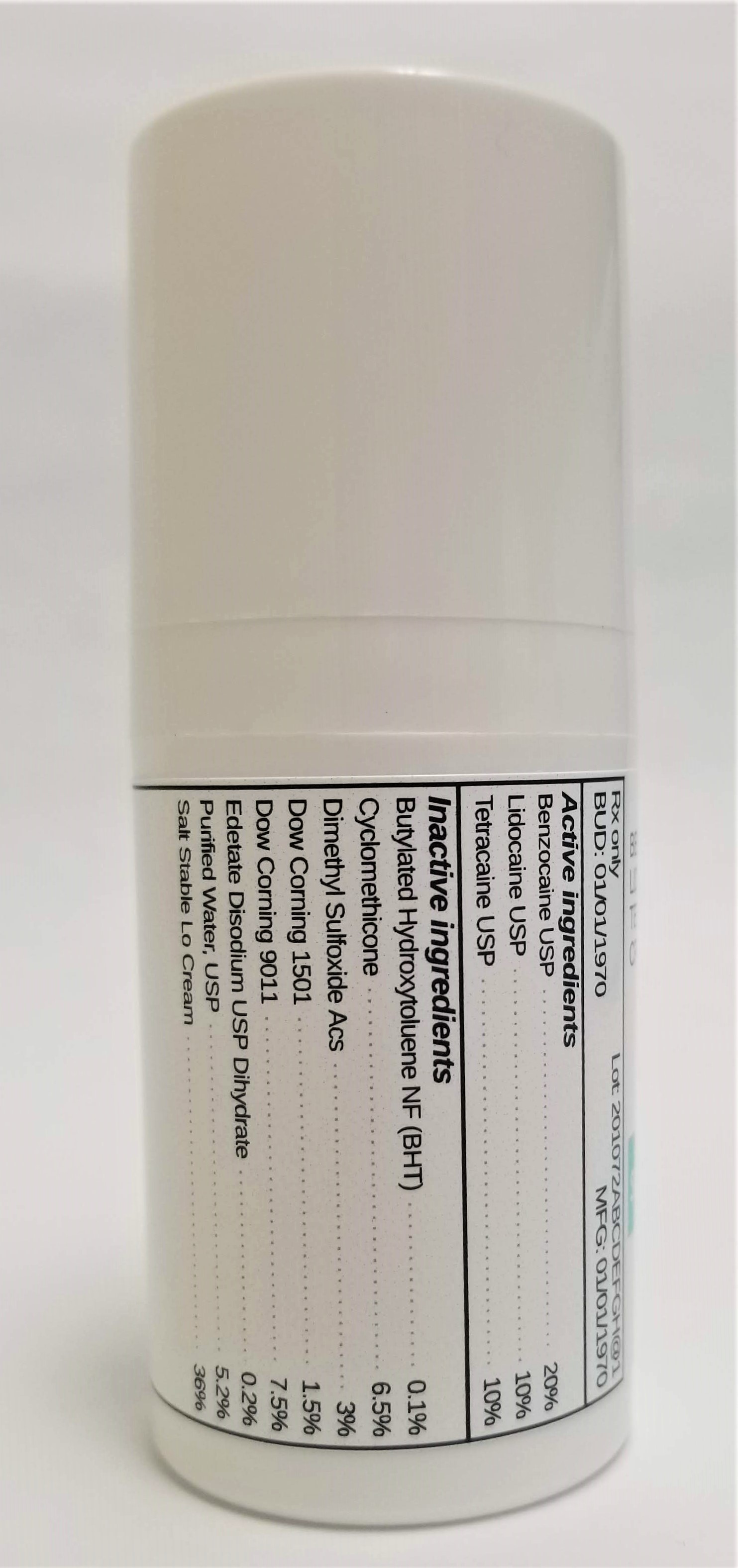 DRUG LABEL: BENZOCAINE 20% / LIDOCAINE 10% / TETRACAINE 10%
NDC: 72934-2009 | Form: CREAM
Manufacturer: Sincerus Florida, LLC
Category: prescription | Type: HUMAN PRESCRIPTION DRUG LABEL
Date: 20190522

ACTIVE INGREDIENTS: BENZOCAINE 20 g/100 g; LIDOCAINE 10 g/100 g; TETRACAINE 10 g/100 g

BENZOCAINE 20% / LIDOCAINE 10% / TETRACAINE 10%